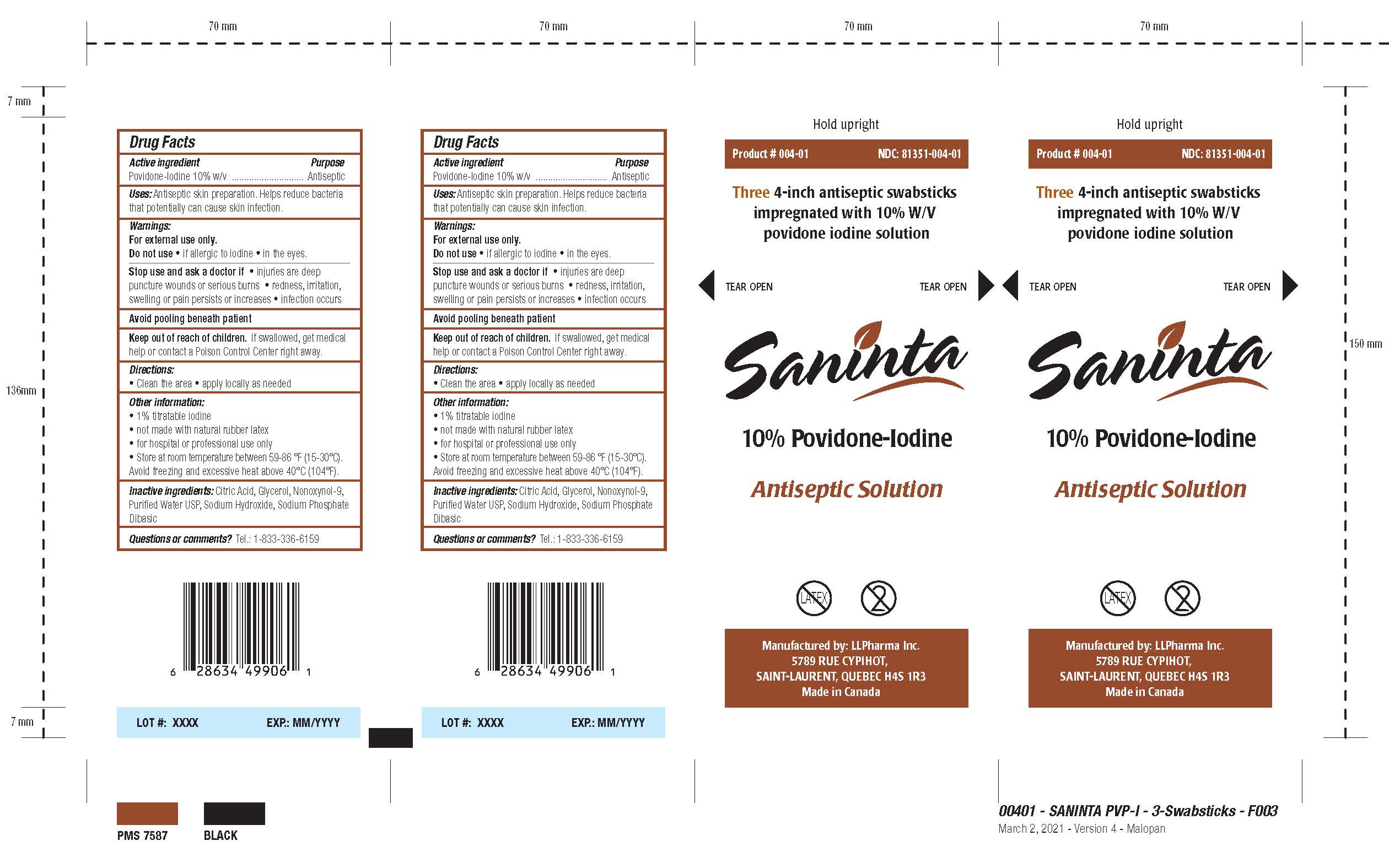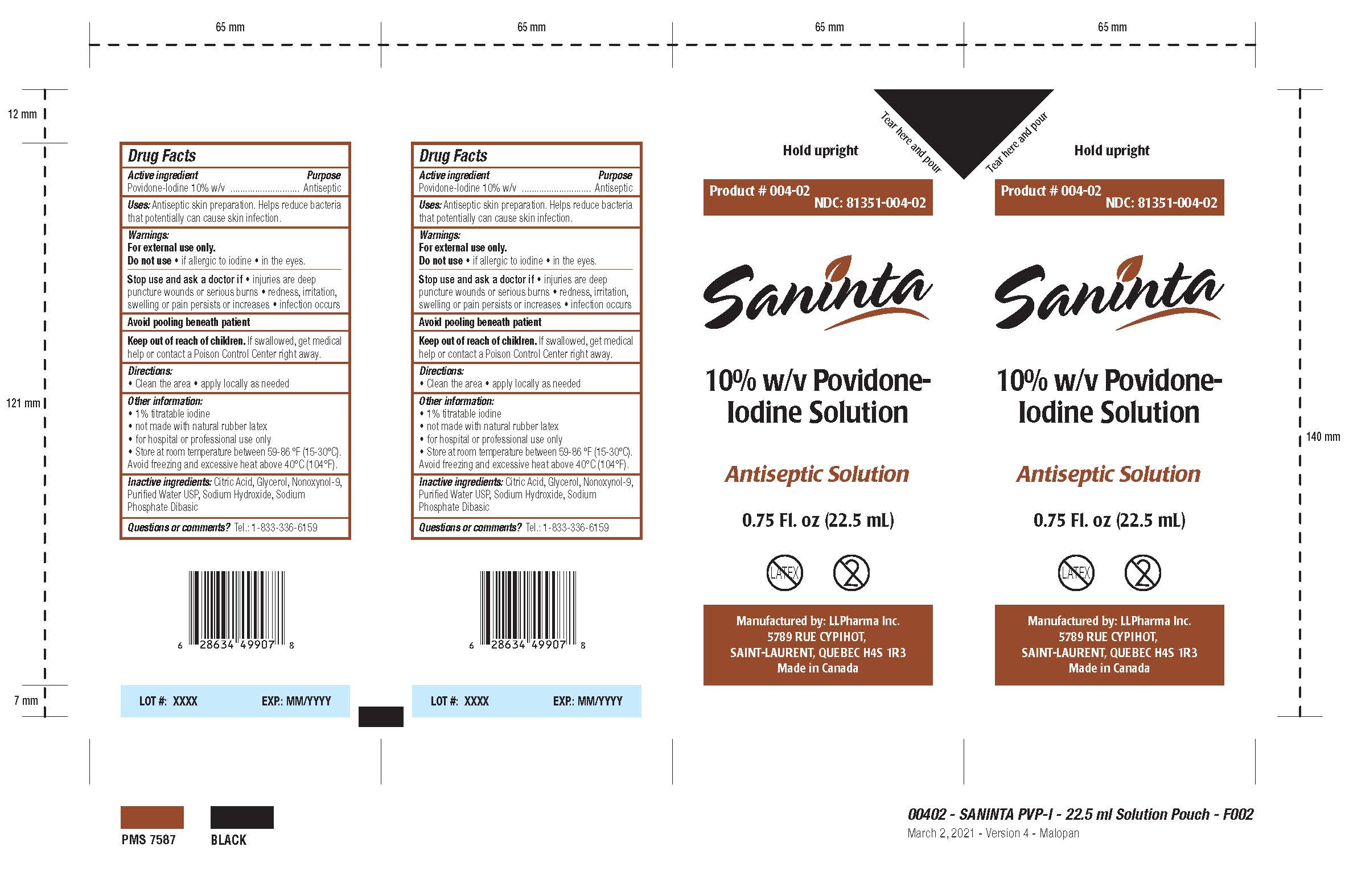 DRUG LABEL: Saninta 10% Povidone-Iodine
NDC: 81351-004 | Form: LIQUID
Manufacturer: LL Pharma
Category: otc | Type: HUMAN OTC DRUG LABEL
Date: 20251231

ACTIVE INGREDIENTS: POVIDONE-IODINE 100 mg/1 mL
INACTIVE INGREDIENTS: WATER; GLYCERIN; NONOXYNOL-9; SODIUM HYDROXIDE; SODIUM PHOSPHATE DIBASIC DIHYDRATE; ANHYDROUS CITRIC ACID

Drug Facts - Saninta 10% w/v Povidone-Iodine Solution

Active Ingredient

Povidone-Iodine 10% w/v

Purpose

Antiseptic

Use

Antiseptic skin preparation. Helps reduce bacteria that potentially can cause skin infection.

Warnings

For external use only.

Do not use

- if allergic to iodine
- in the eyes

Stop use and ask a doctor

Stop use and ask a doctorif

- injuries are deep puncture wounds or serious burns
- redness, irritation, swelling or pain persists or increases
- infection occurs

Avoid pooling beneath patient

Keep out of reach of children. If swallowed, get medical help or contact a Poison Control Center right away.

Directions

- Clean the area.
- apply locally as needed

Other Information

- 1% titratable iodine
- not made with natural rubber latex
- for hospital or professional use only
- Store at room temperature between 59-86ºF (15 - 30ºC).
- Avoid freezing and excessive heat above 40ºC (104ºF).

Inactive ingredients

Citric Acid, Glycerol, Nonoxynol-9, Purified Water USP, Sodium Hydroxide, Sodium Phosphate Dibasic

Questions or Comments? Tel.: 1-833-336-6159

Package Label - Principal Display Panel

NDC: 81351-004-01 / 81351-004-02

Product # 004-01 / 004-02

Hold upright

[Tear here and pour]

[Three 4-inch antiseptic swabsticks impregnated with 10% W/V povidone-iodine solution]

[Tear open]

Saninta

Antiseptic Solution

10% w/v Povidone-Iodine [Solution]

[0.75 Fl.ox (22.5 mL)]

Latex cross-through logo

multiple-use cross-through logo

UPC Code

Manufactured by:

LL Pharma Inc.

5789 rue Cypihot, Saint-Laurent, Quebec H4S 1R3

Made in Canada

www.llpharmainc.com

LOT #: XXXX

EXP.: MM/YYYY